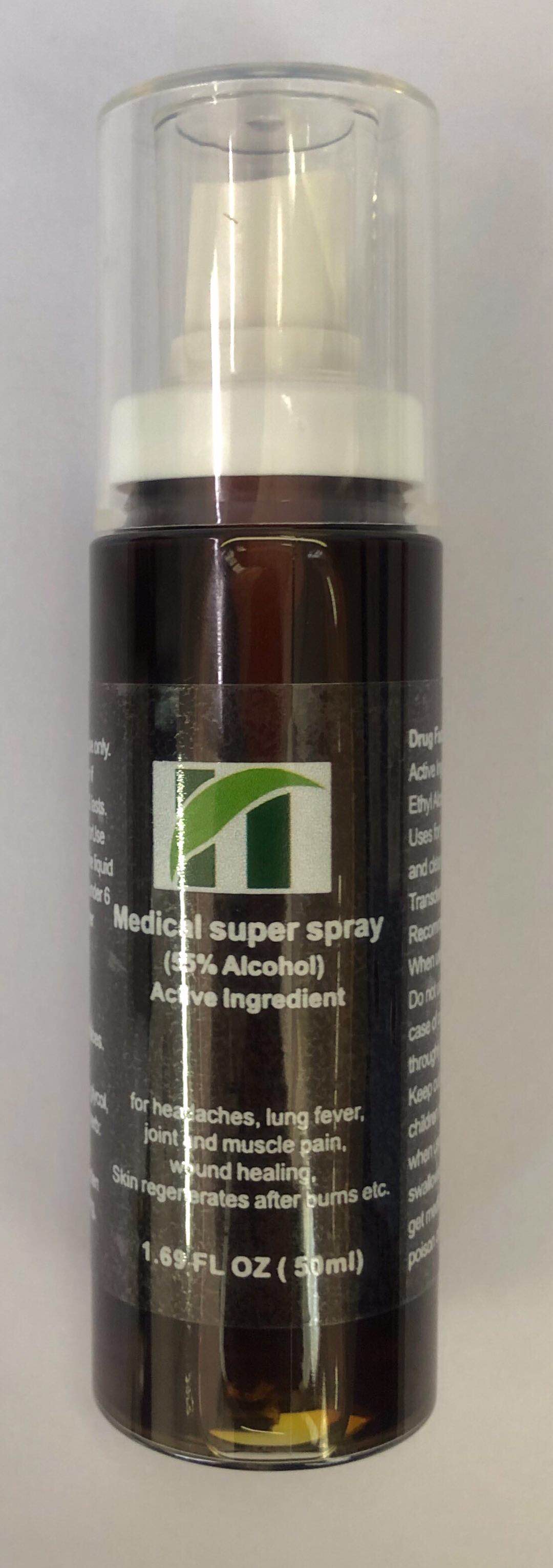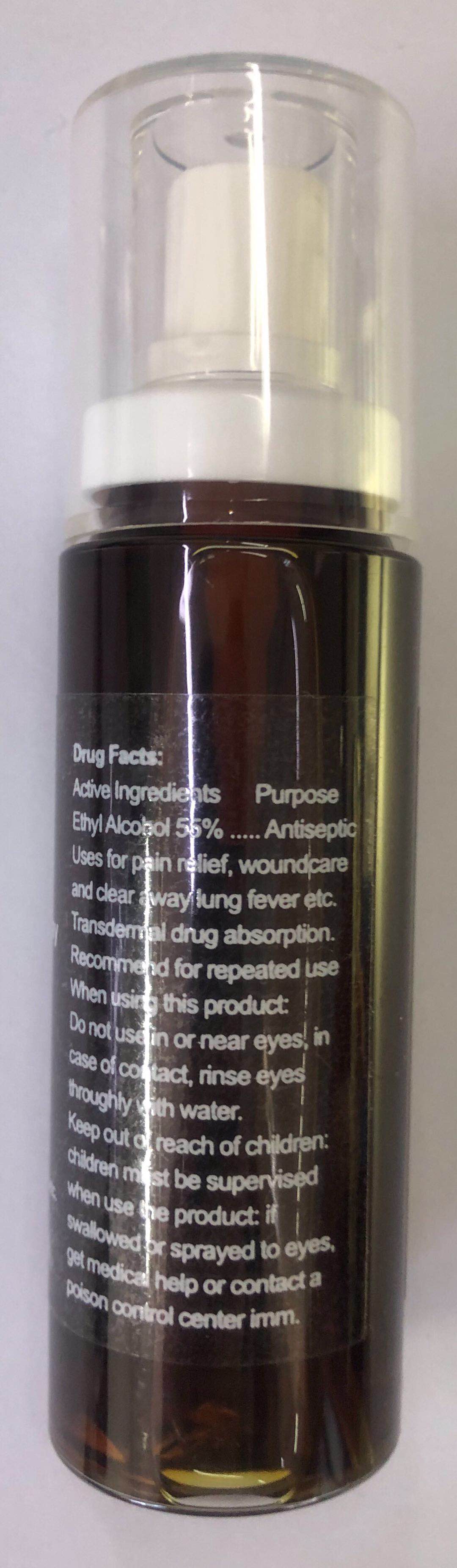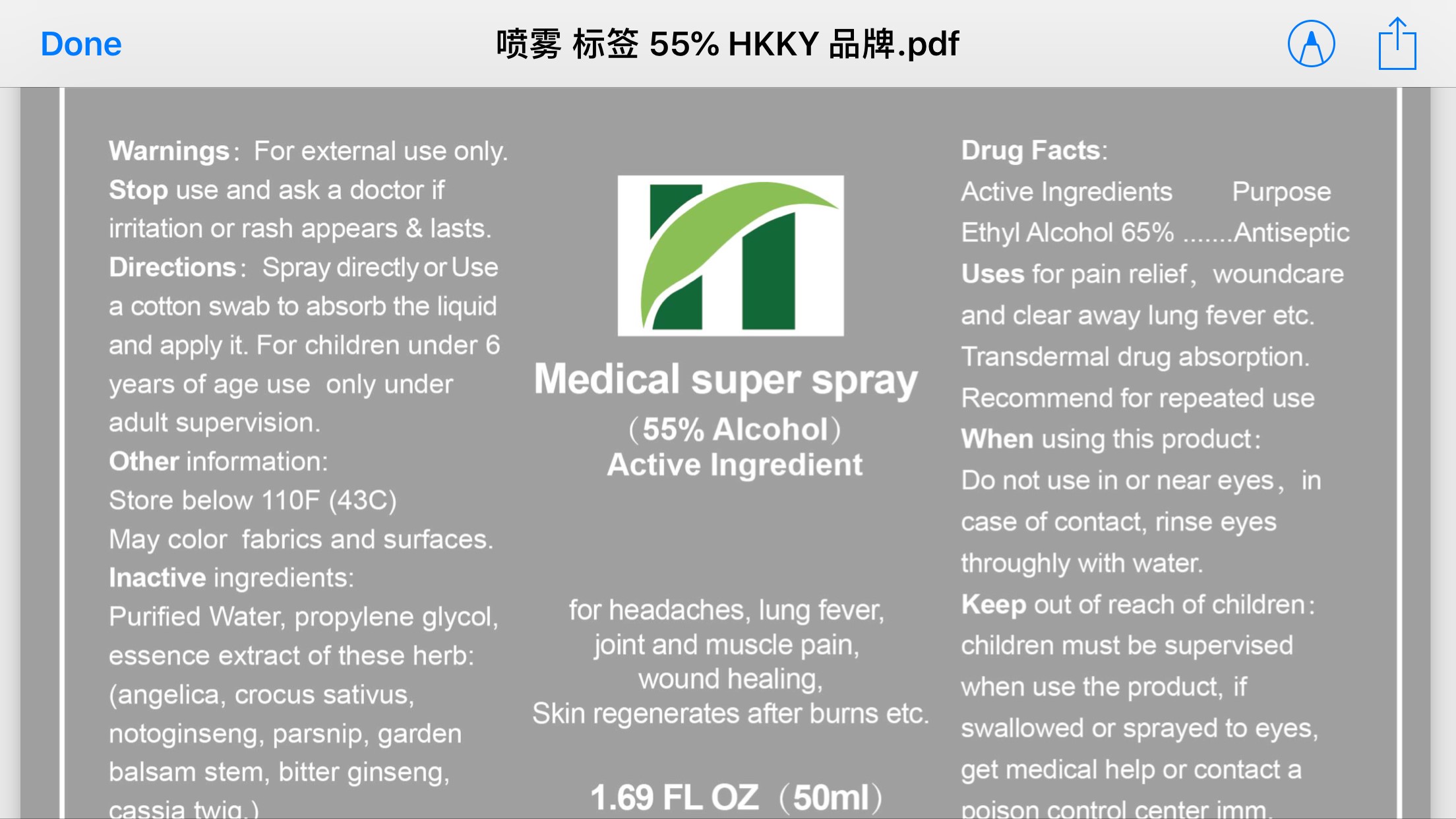 DRUG LABEL: Medical Super
NDC: 71073-302 | Form: SPRAY
Manufacturer: Beijing HKKY Medical Tech. Co., Ltd.
Category: otc | Type: HUMAN OTC DRUG LABEL
Date: 20240113

ACTIVE INGREDIENTS: ALCOHOL 55 mL/100 mL
INACTIVE INGREDIENTS: WATER; CINNAMOMUM CASSIA TWIG; PROPYLENE GLYCOL; CROCUS SATIVUS FLOWER; PANAX NOTOGINSENG ROOT; PARSNIP

71073-302 Medical Super Spray

Active ingredient

Ethyl Alcohol 55%

Purpose

Antiseptic

Uses

For pain relief, wound care and clear away lung fever etc

Transdermal drug absorption

Recommended for repeated use

Warnings

For external use only.

When using this product

• Do not use in or near eyes. In case of contact, rinse eyes thoroughly with water

Stop use and ask a doctor:

if irritation or rash appears and lasts

Keep out of reach of children

Children must be supervised when using this product. If swallowed or sprayed to eyes, get medical help or contact a Poison Control Center immediately.

Directions

Spray directly or use a cotton swab to absorb the liquid and apply it.

For children under 6 years of age, use only under adult supervision

Other information

Store below 110F (43C)

May discolor surfaces and fabrics

Inactive ingredients

Water, Propylene Glycol, Essence Extract of herbs (angelica, cassia twig, crocus sativus, notoginseng, PARSNIP, garden balsam stem, bitterginseng)